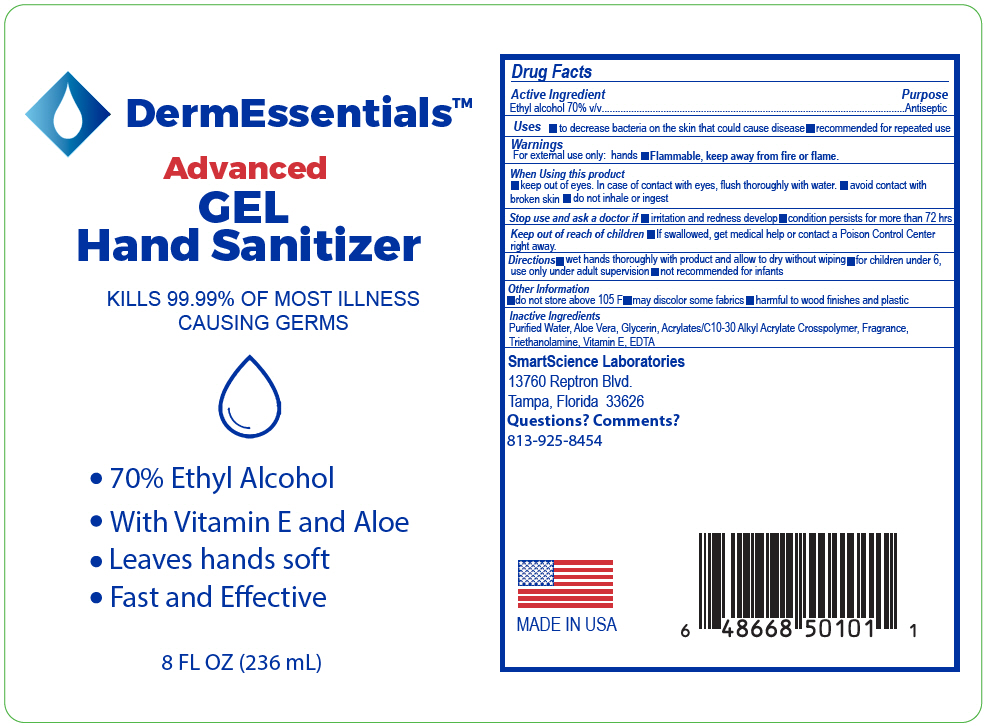 DRUG LABEL: DermEssentials Advanced Hand Sanitizer
NDC: 64479-501 | Form: GEL
Manufacturer: SmartScience Laboratories, Inc.
Category: otc | Type: HUMAN OTC DRUG LABEL
Date: 20200505

ACTIVE INGREDIENTS: ALCOHOL 0.7 mL/1 mL
INACTIVE INGREDIENTS: CARBOMER INTERPOLYMER TYPE A (ALLYL SUCROSE CROSSLINKED); ALOE VERA LEAF; EDETATE DISODIUM ANHYDROUS; .ALPHA.-TOCOPHEROL ACETATE; GLYCERIN; WATER; TROLAMINE; LIMONENE, (+)-

DermEssentials™ Advanced Hand Sanitizer

Drug Facts

Active Ingredient

Ethyl alcohol 70% v/v

Purpose

Antiseptic

Uses

- to decrease bacteria on the skin that could cause disease
- recommended for repeated use

Warnings

For external use only: hands

- Flammable, keep away from fire or flame.

When Using this product

- keep out of eyes. In case of contact with eyes, flush thoroughly with water.
- avoid contact with broken skin
- do not inhale or ingest

Stop use and ask a doctor if

- irritation and redness develop
- condition persists for more than 72 hrs

Keep out of reach of children

- If swallowed, get medical help or contact a Poison Control Center right away.

Directions

- wet hands thoroughly with product and allow to dry without wiping
- for children under 6, use only under adult supervision
- not recommended for infants

Other Information

- do not store above 105 F
- may discolor some fabrics
- harmful to wood finishes and plastic

Inactive Ingredients

Purified Water, Aloe Vera, Glycerin, Acrylates/C10-30 Alkyl Acrylate Crosspolymer, Fragrance, Triethanolamine, Vitamin E, EDTA

Questions? Comments?

813-925-8454

PRINCIPAL DISPLAY PANEL - 236 mL Bottle Label

DermEssentials™

Advanced
GEL
Hand Sanitizer

KILLS 99.99% OF MOST ILLNESS
CAUSING GERMS

- 70% Ethyl Alcohol
- With Vitamin E and Aloe
- Leaves hands soft
- Fast and Effective

8 FL OZ (236 mL)